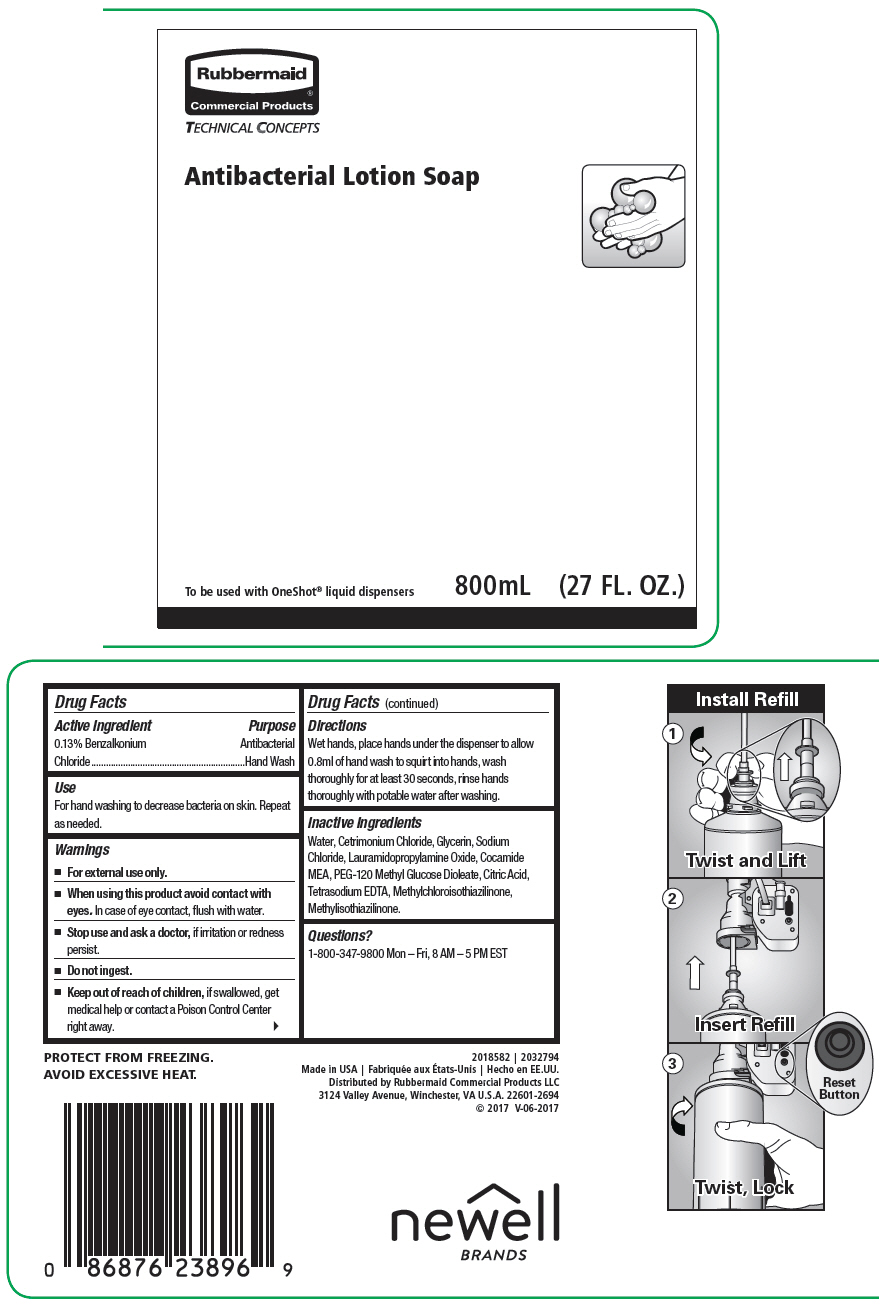 DRUG LABEL: Antibacterial
NDC: 65321-031 | Form: SOAP
Manufacturer: Rubbermaid Commercial Products LLC
Category: otc | Type: HUMAN OTC DRUG LABEL
Date: 20241010

ACTIVE INGREDIENTS: Benzalkonium Chloride 13 mg/10 mL
INACTIVE INGREDIENTS: Water; Cetrimonium Chloride; Glycerin; Sodium Chloride; Lauramidopropylamine Oxide; Coco Monoethanolamide; PEG-120 Methyl Glucose Dioleate; Citric Acid Monohydrate; Edetate Sodium; METHYLCHLOROISOTHIAZOLINONE; METHYLISOTHIAZOLINONE

Antibacterial Lotion Soap

Drug Facts

Active Ingredient

0.13% Benzalkonium Chloride

Purpose

Antibacterial Hand Wash

Use

For hand washing to decrease bacteria on skin. Repeat as needed.

Warnings

- For external use only.

- When using this product avoid contact with eyes. In case of eye contact, flush with water.

- Stop use and ask a doctor, if irritation or redness persist.

- Do not ingest.

- Keep out of reach of children, if swallowed, get medical help or contact a Poison Control Center right away.

Directions

Wet hands, place hands under the dispenser to allow 0.8ml of hand wash to squirt into hands, wash thoroughly for at least 30 seconds, rinse hands thoroughly with potable water after washing.

Inactive Ingredients

Water, Cetrimonium Chloride, Glycerin, Sodium Chloride, Lauramidopropylamine Oxide, Cocamide MEA, PEG-120 Methyl Glucose Dioleate, Citric Acid, Tetrasodium EDTA, Methylchloroisothiazilinone, Methylisothiazilinone.

Questions?

1-800-347-9800 Mon – Fri, 8 AM – 5 PM EST

Distributed by Rubbermaid Commercial Products LLC
3124 Valley Avenue, Winchester, VA U.S.A. 22601-2694

PRINCIPAL DISPLAY PANEL - 800 mL Bottle Label

Rubbermaid®
Commercial Products

TECHNICAL CONCEPTS

Antibacterial Lotion Soap

To be used with OneShot® liquid dispensers
800mL
(27 FL. OZ.)